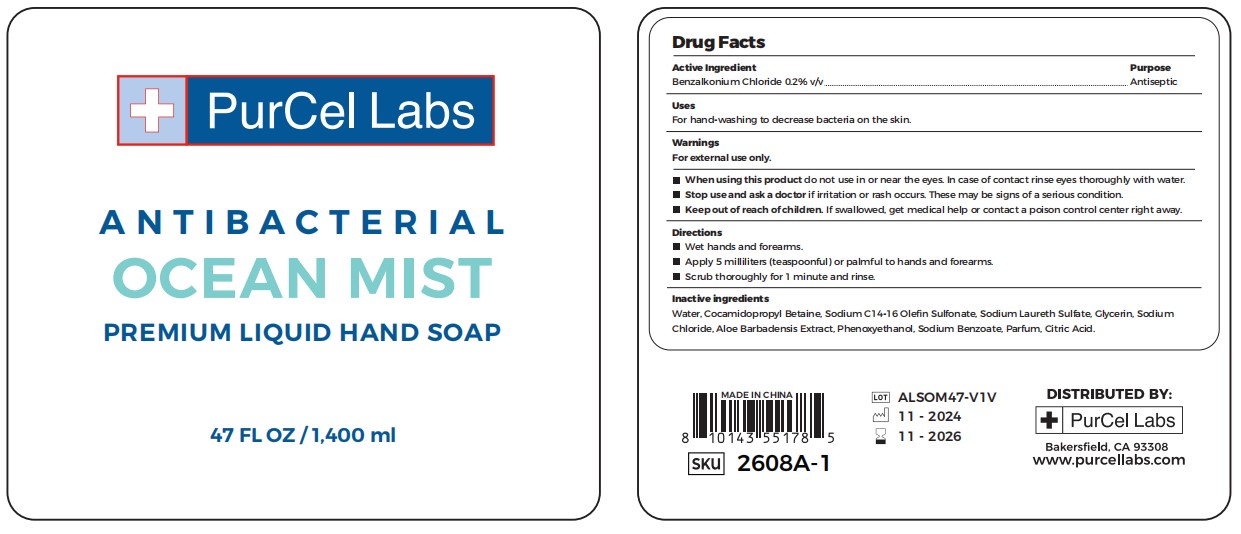 DRUG LABEL: ANTIBACTERIAL washing liquid
NDC: 83584-724 | Form: SOAP
Manufacturer: PurCel Labs LLC
Category: otc | Type: HUMAN OTC DRUG LABEL
Date: 20250112

ACTIVE INGREDIENTS: BENZALKONIUM CHLORIDE 0.2 g/100 mL
INACTIVE INGREDIENTS: CITRIC ACID; SODIUM LAURETH SULFATE; WATER; ALOE VERA LEAF; SODIUM C14-16 OLEFIN SULFONATE; SODIUM BENZOATE; SODIUM CHLORIDE; GLYCERIN; PHENOXYETHANOL; COCAMIDOPROPYL BETAINE

OCEAN MIST LIQUID 83584-724

Active Ingredient

Benzalkonium Chloride 0.2% v/v

Purpose

Antiseptic

Uses

For hand-washing to decrease bacteria on the skin.

Warnings

For external use only

When using this product do not use in or near the eyes. In case of contact rinse eyes thoroughly with water.

Stop use and ask a doctor if irritation or rash occurs. These may be signs of a serious condition.

Keep out of reach of children. If swallowed, get medical help or contact a poison control center right away.

Directions

Wet hands and forearms.
Apply 5 milliliters (teaspoonful) or palmful to hands and forearms.
Scrub thoroughly for 1 minute and rinse.

Inactive ingredients

Water, Cocamidopropyl Betaine, Sodium C14-16 Olefin Sulfonate, Sodium Laureth Sulfate, Glycerin, Sodium
Chloride, Aloe Barbadensis Extract, Phenoxyethanol, Sodium Benzoate, Parfum, Citric Acid.